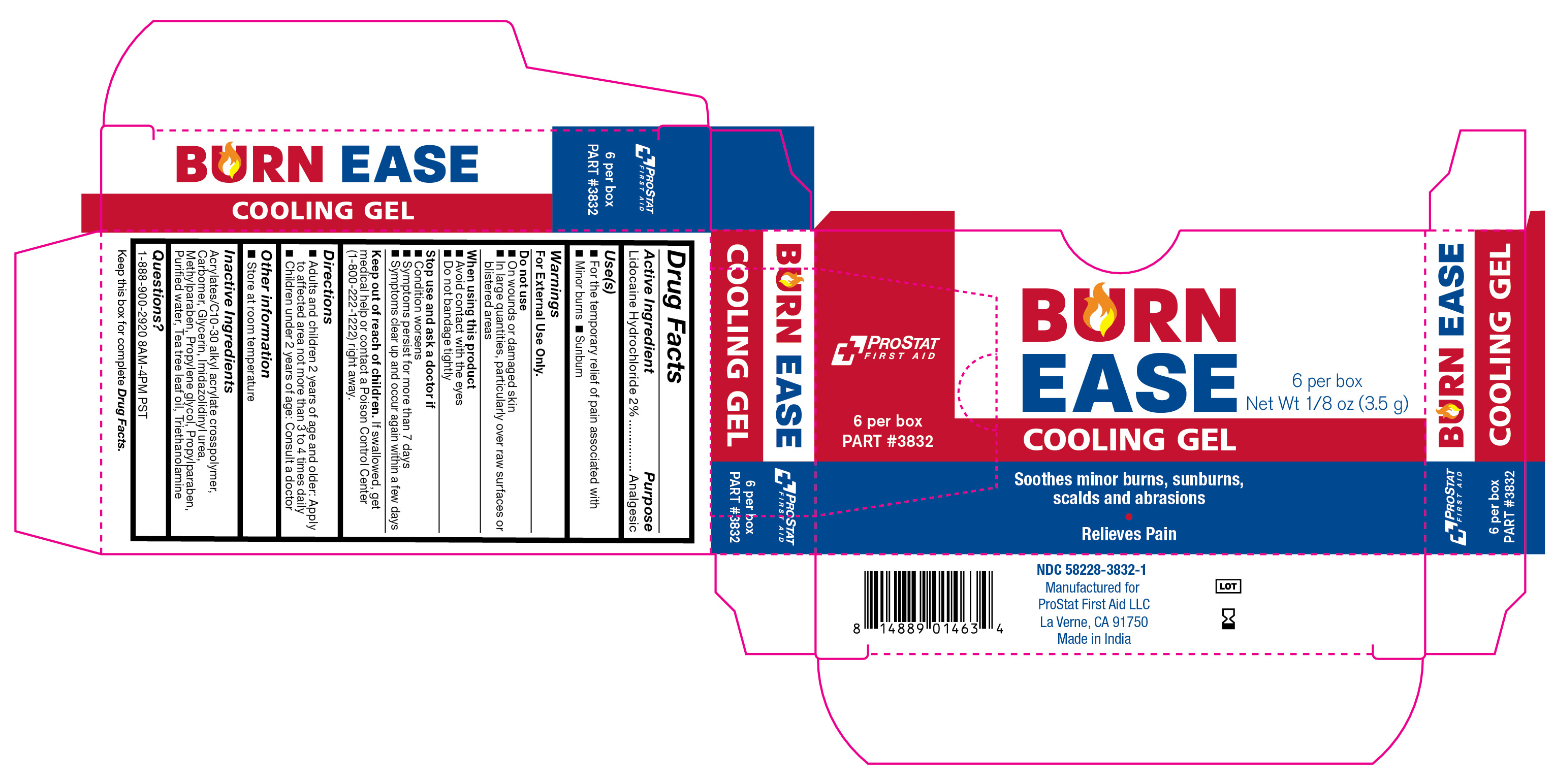 DRUG LABEL: Burn Ease
NDC: 58228-3832 | Form: GEL
Manufacturer: ProStat First Aid LLC
Category: otc | Type: HUMAN OTC DRUG LABEL
Date: 20251215

ACTIVE INGREDIENTS: LIDOCAINE HYDROCHLORIDE 2 g/100 g
INACTIVE INGREDIENTS: CARBOMER COPOLYMER TYPE B (ALLYL PENTAERYTHRITOL CROSSLINKED); IMIDUREA; TROLAMINE; GLYCERIN; METHYLPARABEN; PROPYLPARABEN; WATER; CARBOMER HOMOPOLYMER TYPE C (ALLYL PENTAERYTHRITOL CROSSLINKED); PROPYLENE GLYCOL; TEA TREE OIL

3832 Burn Ease

Active Ingredient

Lidocaine Hydrochloride 2%

Purpose

Analgesic

Use(s)

• For the temporary relief of pain associated with • Minor burns • Sunburn

Warnings

For External Use Only

Do not use

• On wounds or damaged skin

• In large quantities, particularly over raw surfaces or blistered areas

When using this product

• Avoid contact with the eyes

• Do not bandage tightly

Stop use and ask a doctor if

• Condition worsens

• Symptoms persist for more than 7 days

• Symptoms clear up and occur again within a few days

Keep out of reach of children

If swallowed, get medical help or contact a Poison Control Center (1-800-222-1222) right away.

Directions

• Adults and children 2 years of age and older: Apply to affected area not more than 3 to 4 times daily

• Children under 2 years of age: Consult a doctor

Other Information

• Store at room temperature

Inactive Ingredients

Acrylates/C10-30 alkyl acrylate crosspolymer, Carbomer, Glycerin, Imidazolidinyl urea, Methylparaben, Proplyene glycol, Propylparaben, Purified water, Tea tree leaf oil, Triethanolamine

Questions?

1-888-900-2920 8AM-4PM PST

Label

Burn Ease